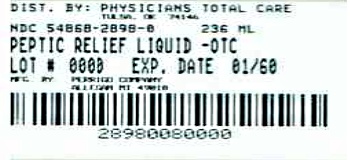 DRUG LABEL: Peptic Relief
NDC: 54868-2898 | Form: LIQUID
Manufacturer: Physicians Total Care, Inc.
Category: otc | Type: HUMAN OTC DRUG LABEL
Date: 20120830

ACTIVE INGREDIENTS: BISMUTH SUBSALICYLATE 262 mg/15 mL
INACTIVE INGREDIENTS: D&C RED NO. 22; D&C RED NO. 28; MAGNESIUM ALUMINUM SILICATE; WATER; SACCHARIN SODIUM DIHYDRATE; SALICYLIC ACID; SODIUM SALICYLATE; SORBIC ACID; XANTHAN GUM

Perrigo Stomach Relief Drug Facts

Active ingredient (in each 15 mL Tablespoon)

Bismuth subsalicylate 262 mg

Purposes

Upset stomach reliever/antidiarrheal

Uses

relieves

- travelers’ diarrhea
- diarrhea
- upset stomach due to overindulgence in food and drink, including:
- heartburn
- indigestion
- nausea
- gas
- belching
- fullness

Warnings

Reye’s syndrome: Children and teenagers who have or are recovering from chicken pox or flu-like symptoms should not use this product. When using this product, if changes in behavior with nausea and vomiting occur, consult a doctor because these symptoms could be an early sign of Reye’s syndrome, a rare but serious illness.

Allergy alert: Contains salicylate. Do not take if you are

- allergic to salicylates (including aspirin)
- taking other salicylate products

Do not use

if you have

- an ulcer
- a bleeding problem
- bloody or black stool

Ask a doctor before use if you have

- fever
- mucus in the stool

Ask a doctor or pharmacist before use if you are

taking any drug for

- anticoagulation (thinning the blood)
- diabetes
- gout
- arthritis

When using this product

a temporary, but harmless, darkening of the stool and/or tongue may occur

Stop use and ask a doctor if

- symptoms get worse
- ringing in the ears or loss of hearing occurs
- diarrhea lasts more than 2 days

If pregnant or breast-feeding,

ask a health professional before use.

Keep out of reach of children.

In case of overdose, get medical help or contact a Poison Control Center right away. (1-800-222-1222)

Directions

- shake well before use
- for accurate dosing, use dose cup
- adults and children 12 years and over: 1 dose (2 Tbsp or 30 mL) every 1/2 to 1 hour as needed
- do not exceed 8 doses (16 Tbsp or 240 mL) in 24 hours
- use until diarrhea stops but not more than 2 days
- children under 12 years: ask a doctor
- drink plenty of clear fluids to help prevent dehydration caused by diarrhea

Other information

- each Tbsp contains: magnesium 5 mg, potassium 5 mg and sodium 5 mg
- salicylate 123 mg
- protect from freezing
- sugar free
- low sodium
- store at 20°-25°C (68°-77°F)
- does not meet USP requirements for pH
- for health information visit www.more-info.info

Inactive ingredients

D&C red #22, D&C red #28, flavor, magnesium aluminum silicate, methylcellulose, purified water, saccharin sodium, salicylic acid, sodium salicylate, sorbic acid, xanthan gum

Questions or comments?

1-800-719-9260

Additional barcode labeling by:
Physicians Total Care, Inc.
Tulsa, Oklahoma 74146

Principal Display Panel

Original Strength

Stomach Relief

Bismuth Subsalicylate 262 mg

Antidiarrheal/Upset Stomach Reliever

Protective Coating Action

Soothing Relief for 5 Symptoms:

- Upset Stomach
- Indigestion
- Heartburn
- Nausea
- Diarrhea

Compare to active ingredient of Pepto-Bismol®

NDC 54868-2898-0
237 mL

Stomach Relief Label